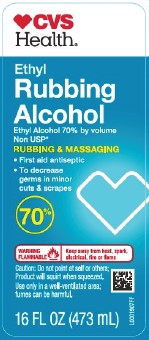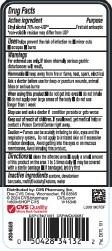 DRUG LABEL: Ethyl Rubbing Alcohol
NDC: 59779-164 | Form: LIQUID
Manufacturer: CVS Pharmacy, Inc.
Category: otc | Type: HUMAN OTC DRUG LABEL
Date: 20260203

ACTIVE INGREDIENTS: ALCOHOL 70 mL/100 mL
INACTIVE INGREDIENTS: ACETONE; DENATONIUM BENZOATE; METHYL ISOBUTYL KETONE; WATER

CVS 876.002/876AC
Ethyl Rubbing Alcohol 70%

Active ingredient

Ethyl alcohol 70% non-USP*

*non-volatile residue may differ from USP

Purpose

First aid antiseptic

Uses

helps prevent the risk of infection in:

- minor cuts
- scrapes
- burns

Warnings

For external use only. If taken internally serious gastric disturbances will result.

Flammable. Keep away from fire or flame, heat, spark, electrical

Ask a doctor before use

for deep or puncture wounds, animal bites or serious burns

When using this product

- do not get into eyes
- do not inhale
- do not apply over large areas of the body
- do not use longer than 1 week

Stop use and ask a doctor if

condition persists or gets worse

Keep out of reach of children.

If swallowed, get medical help or contact a Poison Control Center right away.

Caution

Fumes can be acutely irritating to skin, eyes and the respiratory system. Do not apply to irritated skin or if excessive irritation develops. Avoid getting into the eyes or on mucous membranes. Avoid inhaling this product.

Directions

- clean the affected area
- apply a small amount of this product on the affected area 1 to 3 times daily
- may be covered with a sterile bandage
- if bandage, let dry first

Inactive ingredients

acetone, denatonium benzoate, methyl isobutyl ketone, water

Adverse reaction

Distributed by: CVS Pharmacy, Inc.

One CVS Drive, Woonsocket, RI 02895

© 2024 CVS/pharmacy CVS.com

1-800-SHOP CVS

CVS Quality

Money Back Guarantee

DSP-TN-21091 DSP-MO-20087

Pat. D675, 101

Principal display panel

CVS Health®

Ethyl Rubbing Alcohol

Ethyl Alcohol 70% by volume

Non USP*

RUBBING & MASSAGING

- First aid antiseptic
- To decrease germs in minor cuts & scrapes

70%

WARNING FLAMMABLE - Keep away from heat, spark, electrical, fire or flame

Caution: Do not point at self or others; Product will squirt when squeezed

Use only in a well-ventilated area; fumes may be harmful

16 FL OZ (473 mL)